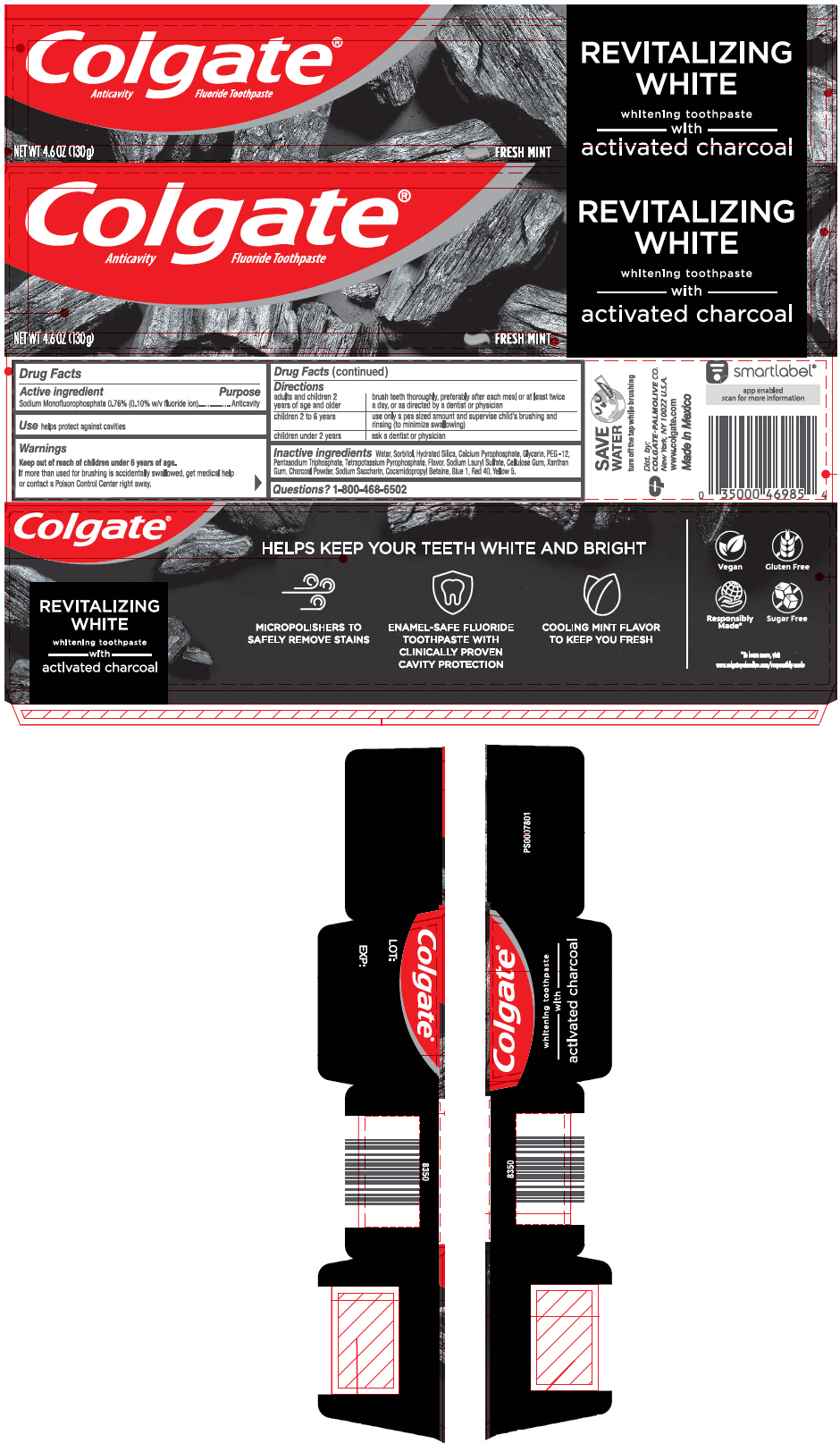 DRUG LABEL: Colgate Essentials
NDC: 35000-974 | Form: PASTE, DENTIFRICE
Manufacturer: Colgate-Palmolive Company
Category: otc | Type: HUMAN OTC DRUG LABEL
Date: 20191220

ACTIVE INGREDIENTS: SODIUM MONOFLUOROPHOSPHATE 1 mg/1 g
INACTIVE INGREDIENTS: WATER 181.01 mg/1 g; HYDRATED SILICA; SORBITOL; CALCIUM PYROPHOSPHATE; GLYCERIN; POLYETHYLENE GLYCOL 600; SODIUM TRIPOLYPHOSPHATE ANHYDROUS; POTASSIUM PYROPHOSPHATE; SODIUM LAURYL SULFATE; CARBOXYMETHYLCELLULOSE SODIUM, UNSPECIFIED; SACCHARIN SODIUM; ACTIVATED CHARCOAL; XANTHAN GUM; COCAMIDOPROPYL BETAINE; FD&C BLUE NO. 1; FD&C RED NO. 40; FD&C YELLOW NO. 5

Colgate® Essentials™ Toothpaste

Drug Facts

Active ingredient

Sodium monofluorophosphate 0.76% (0.10% w/v fluoride ion)

Purpose

Anticavity

Use

helps protect against cavities

Warnings

Keep out of reach of children under 6 years of age.

If more than used for brushing is accidentally swallowed, get medical help or contact a Poison Control Center right away.

Directions

adults and children 2 years of age and older | brush teeth thoroughly, preferably after each meal or at least twice a day, or as directed by a dentist or physician
children 2 to 6 years | use only a pea sized amount and supervise child's brushing and rinsing (to minimize swallowing)
children under 2 years | ask a dentist or physician

Inactive ingredients

water, hydrated silica, sorbitol, calcium pyrophosphate, glycerin, PEG-12, pentasodium triphosphate, tetrapotassium pyrophosphate, flavor, sodium lauryl sulfate, cellulose gum, sodium saccharin, charcoal powder, xanthan gum, cocamidopropyl betaine, blue 1, red 40, yellow 5

Questions?

1-800-468-6502

Dist. by:
COLGATE-PALMOLIVE COMPANY
New York, NY 10022 U.S.A.

PRINCIPAL DISPLAY PANEL - 130 g Tube Carton

Colgate®
Anticavity Fluoride Toothpaste

REVITALIZING
WHITE

whitening toothpaste
with
activated charcoal

NET WT 4.6 OZ (130g)
FRESH MINT